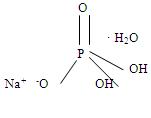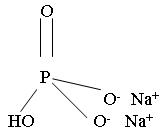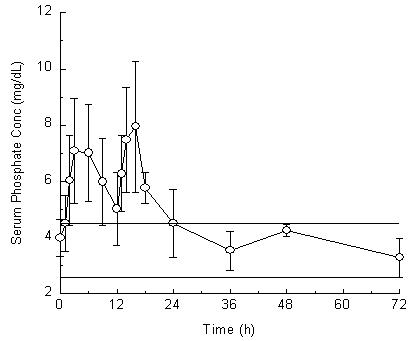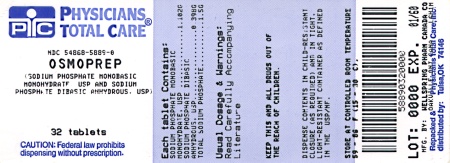 DRUG LABEL: OsmoPrep
NDC: 54868-5889 | Form: TABLET
Manufacturer: Physicians Total Care, Inc.
Category: prescription | Type: HUMAN PRESCRIPTION DRUG LABEL
Date: 20100604

ACTIVE INGREDIENTS: SODIUM PHOSPHATE, MONOBASIC, MONOHYDRATE 1.102 g/1 1; SODIUM PHOSPHATE, DIBASIC ANHYDROUS 0.398 g/1 1
INACTIVE INGREDIENTS: POLYETHYLENE GLYCOL 8000; MAGNESIUM STEARATE

WARNINGS

There have been rare, but serious reports of acute phosphate nephropathy in patients who received oral sodium phosphate products for colon cleansing prior to colonoscopy. Some cases have resulted in permanent impairment of renal function and some patients required long-term dialysis. While some cases have occurred in patients without identifiable risk factors, patients at increased risk of acute phosphate nephropathy may include those with increased age, hypovolemia, increased bowel transit time (such as bowel obstruction), active colitis, or baseline kidney disease, and those using medicines that affect renal perfusion or function (such as diuretics, angiotensin converting enzyme [ACE] inhibitors, angiotensin receptor blockers [ARBs], and possibly nonsteriodal anti-inflammatory drugs [NSAIDs]).
See WARNINGS.
It is important to use the dose and dosing regimen as recommended (pm/am split dose).
See DOSAGE and ADMINISTRATION.

DESCRIPTION

OsmoPrep® (sodium phosphate monobasic monohydrate, USP, and sodium phosphate dibasic anhydrous, USP) is a purgative used to clean the colon prior to colonoscopy. OsmoPrep is manufactured with a highly soluble tablet binder and does not contain microcrystalline cellulose (MCC). OsmoPrep Tablets are oval, white to off-white compressed tablets, debossed with “SLX” on one side of the bisect and “102” on the other side of the bisect. Each OsmoPrep tablet contains 1.102 grams of sodium phosphate monobasic monohydrate, USP and 0.398 grams of sodium phosphate dibasic anhydrous, USP for a total of 1.5 grams of sodium phosphate per tablet. Inert ingredients include polyethylene glycol 8000, NF; and magnesium stearate, NF. OsmoPrep is gluten-free.

The structural and molecular formulae and molecular weights of the active ingredients are shown below:

- Sodium phosphate monobasic monohydrate, USP
  Molecular Formula: NaH2PO4 • H2O
  Molecular Weight: 137.99
- Sodium phosphate dibasic anhydrous, USP
  Molecular Formula: Na2HPO4
  Molecular Weight: 141.96

OsmoPrep Tablets are for oral administration only.

CLINICAL PHARMACOLOGY

OsmoPrep Tablets, a dosing regimen containing 48 grams of sodium phosphate (32 tablets), induces diarrhea, which effectively cleanses the entire colon. Each administration has a purgative effect for approximately 1 to 3 hours. The primary mode of action is thought to be through the osmotic effect of sodium, causing large amounts of water to be drawn into the colon, promoting evacuation.

Pharmacokinetics

Pharmacokinetic studies with OsmoPrep have not been conducted. However, the following pharmacokinetic study was conducted with Visicol® tablets which contain the same active ingredients (sodium phosphate) as OsmoPrep. In addition, Visicol is administered at a dose that is 25% greater than the OsmoPrep dose.

An open-label pharmacokinetic study of Visicol in healthy volunteers was performed to determine the concentration-time profile of serum inorganic phosphorus levels after Visicol administration. All subjects received the approved Visicol dosing regimen (60 grams of sodium phosphate with a total liquid volume of 3.6 quarts) for colon cleansing. A 30 gram dose (20 tablets given as 3 tablets every 15 minutes with 8 ounces of clear liquids) was given beginning at 6 PM in the evening. The 30 gram dose (20 tablets given as 3 tablets every 15 minutes with 8 ounces of clear liquids) was repeated the following morning beginning at 6 AM.

Twenty-three healthy subjects (mean age 57 years old; 57% male and 43% female; and 65% Hispanic, 30% Caucasian, and 4% African-American) participated in this pharmacokinetic study. The serum phosphorus level rose from a mean (± standard deviation) baseline of 4.0 (± 0.7) mg/dL to 7.7 (± 1.6 mg/dL), at a median of 3 hours after the administration of the first 30-gram dose of sodium phosphate tablets (see Figure 1). The serum phosphorus level rose to a mean of 8.4 (± 1.9) mg/dL, at a median of 4 hours after the administration of the second 30-gram dose of sodium phosphate tablets. The serum phosphorus level remained above baseline for a median of 24 hours after the administration of the initial dose of sodium phosphate tablets (range 16 to 48 hours).

Figure 1. Mean (± standard deviation) serum phosphorus concentrations

The upper (4.5 mg/dL) and lower (2.6 mg/dL) reference limits for serum phosphate are represented by solid bars.

Special Populations

Renal Insufficiency: The effect of renal dysfunction on the pharmacokinetics of OsmoPrep Tablets has not been studied. Since the inorganic form of phosphate in the circulating plasma is excreted almost entirely by the kidneys, patients with renal disease may have difficulty excreting a large phosphate load. Thus, OsmoPrep Tablets should be used with caution in patients with impaired renal function (see WARNINGS).

Hepatic Insufficiency: OsmoPrep Tablets have not been investigated in patients with hepatic failure.

Geriatric: In a single pharmacokinetic study of sodium phosphate tablets, which included 6 elderly volunteers, plasma half-life increased two-fold in subjects greater than 70 years of age compared to subjects less than 50 years of age (3 subjects and 5 subjects, respectively).

Gender: No difference in serum phosphate AUC values were observed in the single pharmacokinetic study conducted with sodium phosphate tablets in 13 male and 10 female healthy volunteers.

CLINICAL STUDIES

The colon cleansing efficacy and safety of OsmoPrep was evaluated in 2 randomized, investigator-blinded, actively controlled, multicenter, U.S. trials in patients scheduled to have an elective colonoscopy. The trials consisted of a dose ranging and a confirmatory phase 3 study.

In the phase 3 trial, patients were randomized into one of the following three sodium phosphate treatment groups: 1) Visicol containing 60 grams of sodium phosphate given in split doses (30 grams in the evening before the colonoscopy and 30 grams on the next day) with at least 3.6 quarts of clear liquids; 2) OsmoPrep containing 60 grams of sodium phosphate given in split doses (30 grams in the evening before the colonoscopy and 30 grams on the next day) with 2.5 quarts of clear liquids; and 3) OsmoPrep containing 48 grams of sodium phosphate (30 grams in the evening before the colonoscopy and 18 grams on the next day) with 2 quarts of clear liquids. Patients were instructed to eat a light breakfast before noon on the day prior to the colonoscopy and then were told to drink only clear liquids after noon on the day prior to the colonoscopy.

The primary efficacy endpoint was the overall colon cleansing response rate in the 4-point Colonic Contents Scale. Response was defined as a rating of “excellent” or “good” on the 4-point scale as determined by the blinded colonoscopist. This phase 3 study was planned to assess the non-inferiority of the two OsmoPrep groups compared to the Visicol group.

The efficacy analysis included 704 adult patients who had an elective colonoscopy. Patients ranged in age from 21 to 89 years old (mean age 56 years old) with 55% female and 45% male patients. Race was distributed as follows: 87% Caucasian, 10% African American, and 3% other race. The OsmoPrep 60 gram and 48 gram treatment groups demonstrated non-inferiority compared to Visicol. See Table 1 for the results.

Table 1: Phase 3 Study – Overall Colon Content Cleansing Response Rates1
Treatment Arm (grams of sodium phosphate) | No. of tablets taken at 6 PM on the day prior to colonoscopy | No. of tablets taken the next day^2 | Excellent | Good | Fair | Inadequate | Overall Response Rate (Excellent or Good)
OsmoPrep 32 tabs (48 g) n = 236 | 20 | 12 | 76% | 19% | 3% | 2% | 95%
OsmoPrep 40 tabs (60 g) n = 233 | 20 | 20 | 73% | 24% | 2% | 1% | 97%
Visicol 40 tabs (60 g) n = 235 | 20 | 20 | 51% | 43% | 6% | 0% | 94%

^1 Colon-cleansing efficacy was based on response rate to treatment. A patient was considered to be a responder if overall colon cleansing was rated as “excellent” or “good” on a 4-point scale based on the amount of retained “colonic contents.” Excellent was defined as greater than 90% of mucosa seen, mostly liquid stool, minimal suctioning needed for adequate visualization. Good was defined as greater than 90% of mucosa seen, mostly liquid stool, significant suctioning needed for adequate visualization. Fair was defined as greater than 90% of mucosa seen, mixture of liquid and semisolid stool, could be suctioned and/or washed. Inadequate was defined as less than 90% of mucosa seen, mixture of semisolid and solid stool which could not be suctioned or washed.
^2 On the day of the colonoscopy, study medication was taken 3 to 5 hours before the start of the colonoscopy.
the day of the colonoscopy, study medication was taken 3 to 5 hours before the start of the colonoscopy.

INDICATIONS AND USAGE

OsmoPrep Tablets are indicated for cleansing of the colon as a preparation for colonoscopy in adults 18 years of age or older.

CONTRAINDICATIONS

OsmoPrep Tablets are contraindicated in patients with biopsy-proven acute phosphate nephropathy.

OsmoPrep Tablets are contraindicated in patients with a known allergy or hypersensitivity to sodium phosphate salts or any of its ingredients.

WARNINGS

Administration of sodium phosphate products prior to colonoscopy for colon cleansing has resulted in fatalities due to significant fluid shifts, severe electrolyte abnormalities, and cardiac arrhythmias. These fatalities have been observed in patients with renal insufficiency, in patients with bowel perforation, and in patients who misused or overdosed sodium phosphate products. It is recommended that patients receiving OsmoPrep be advised to adequately hydrate before, during, and after the use of OsmoPrep.

Considerable caution should be advised before OsmoPrep Tablets are used in patients with the following illnesses: severe renal insufficiency (creatinine clearance less than 30 mL/minute), congestive heart failure, ascites, unstable angina, gastric retention, ileus, acute bowel obstruction, pseudo-obstruction of the bowel, severe chronic constipation, bowel perforation, acute colitis, toxic megacolon, gastric bypass or stapling surgery, or hypomotility syndrome.

Consider performing baseline and post-colonoscopy labs (phosphate, calcium, potassium, sodium, creatinine, and BUN) in patients who may be at increased risk for serious adverse events, including those with history of renal insufficiency, history of-or at greater risk of-acute phosphate nephropathy, known or suspected electrolyte disorders, seizures, arrhythmias, cardiomyopathy, prolonged QT, recent history of a MI and those with known or suspected hyperphosphatemia, hypocalcemia, hypokalemia, and hypernatremia. Also if patients develop vomiting and/or signs of dehydration then measure post-colonoscopy labs (phosphate, calcium, potassium, sodium, creatinine, and BUN).

Renal Disease, Acute Phosphate Nephropathy, and Electrolyte Disorders

There have been rare, but serious, reports of renal failure, acute phosphate nephropathy, and nephrocalcinosis in patients who received oral sodium phosphate products (including oral sodium phosphate solutions and tablets) for colon cleansing prior to colonoscopy. These cases often resulted in permanent impairment of renal function and several patients required long-term dialysis. The time to onset is typically within days; however, in some cases, the diagnosis of these events has been delayed up to several months after the ingestion of these products. Patients at increased risk of acute phosphate nephropathy may include patients with the following: hypovolemia, baseline kidney disease, increased age, and patients using medicines that affect renal perfusion or function [such as diuretics, angiotensin converting enzyme (ACE)inhibitors, angiotensin receptor blockers, and possibly nonsteroidal anti-inflammatory drugs (NSAIDs).

Use OsmoPrep with caution in patients with impaired renal function, patients with a history of acute phosphate nephropathy, known or suspected electrolyte disturbances (such as dehydration), or people taking concomitant medications that may affect electrolyte levels (such as diuretics). Patients with electrolyte abnormalities such as hypernatremia, hyperphosphatemia, hypokalemia, or hypocalcemia should have their electrolytes corrected before treatment with OsmoPrep Tablets.

Seizures

There have been rare reports of generalized tonic-clonic seizures and/or loss of consciousness associated with use of sodium phosphate products in patients with no prior history of seizures. The seizure cases were associated with electrolyte abnormalities (e.g., hyponatremia, hypokalemia, hypocalcemia, and hypomagnesemia) and low serum osmolality. The neurologic abnormalities resolved with correction of fluid and electrolyte abnormalities. OsmoPrep should be used with caution in patients with a history of seizures and in patients at higher risk of seizure [patients using concomitant medications that lower the seizure threshold (such as tricyclic antidepressants), patients withdrawing from alcohol or benzodiazepines, or patients with known or suspected hyponatremia].

Cardiac Arrhythmias

There have been rare, but serious, reports of arrhythmias associated with the use of sodium phosphate products. OsmoPrep should be used with caution in patients with higher risk of arrhythmias (patients with a history of cardiomyopathy, patients with prolonged QT, patients with a history of uncontrolled arrhythmias, and patients with a recent history of a myocardial infarction). Pre-dose and post-colonoscopy ECGs should be considered in patients with high risk of serious, cardiac arrhythmias.

PRECAUTIONS

General

Patients should be instructed to drink 8 ounces of clear liquids with each 4-tablet dose of OsmoPrep Tablets. Patients should take a total of 2 quarts of clear liquids with OsmoPrep. Inadequate fluid intake, as with any effective purgative, may lead to excessive fluid loss, hypovolemia, and dehydration. Dehydration from purgation may be exacerbated by inadequate oral fluid intake, vomiting, and/or use of diuretics.

Patients should be instructed not to administer additional laxative or purgative agents, particularly additional sodium phosphate-based purgative or enema products.

Prolongation of the QT interval has been observed in some patients who were dosed with sodium phosphate colon preparations. QT prolongation with sodium phosphate tablets has been associated with electrolyte imbalances, such as hypokalemia and hypocalcemia. OsmoPrep Tablets should be used with caution in patients who are taking medications known to prolong the QT interval, since serious complications may occur. Pre-dose and post-colonoscopy ECGs should be considered in patients with known prolonged QT.

Administration of OsmoPrep Tablets may induce colonic mucosal aphthous ulcerations, since this endoscopic finding was observed with other sodium phosphate cathartic preparations. In the OsmoPrep clinical program, aphthous ulcers were observed in 3% of patients who took the 48 gram OsmoPrep dosing regimen. This colonoscopic finding should be considered in patients with known or suspected inflammatory bowel disease.

Because published data suggest that sodium phosphate absorption may be enhanced in patients experiencing an acute exacerbation of chronic inflammatory bowel disease, OsmoPrep Tablets should be used with caution in such patients.

Drug Interactions

Medications administered in close proximity to OsmoPrep Tablets may not be absorbed from the gastrointestinal tract due to the rapid intestinal peristalsis and watery diarrhea induced by the purgative agent.

Carcinogenesis, Mutagenesis, Impairment of Fertility

Long-term studies in animals have not been performed to evaluate the carcinogenic potential of OsmoPrep. Studies to evaluate the effect of OsmoPrep on fertility or its mutagenic potential have not been performed.

Pregnancy. Teratogenic Effects: Pregnancy Category C

Animal reproduction studies have not been conducted with OsmoPrep. It is not known whether OsmoPrep can cause fetal harm when administered to a pregnant woman, or can affect reproduction capacity. OsmoPrep Tablets should be given to a pregnant woman only if clearly needed.

Pediatric Use

The safety and efficacy of OsmoPrep Tablets have not been demonstrated in patients less than 18 years of age.

Geriatric Use

In controlled colon preparation trials of OsmoPrep, 228 (24%) of 931 patients were 65 years of age or older. In addition, 49 (5%) of the 931 patients were 75 years of age or older.

Of the 228 geriatric patients in the trials, 134 patients (59%) received at least 48 grams of OsmoPrep. Of the 49 patients 75 years old or older in the trials, 27 (55%) patients received at least 48 grams of OsmoPrep. No overall differences in safety or effectiveness were observed between geriatric patients and younger patients. However, the mean phosphate levels in geriatric patients were greater than the phosphate levels in younger patients after OsmoPrep administration. The mean colonoscopy-day phosphate levels in patients 18-64, 65-74, and ≥ 75 years old who received 48 grams of OsmoPrep in the phase 3 study were 7.0, 7.3, and 8.0 mg/dL, respectively. In addition, in all three sodium phosphate treatment groups, the mean phosphate levels in patients 18-64, 65-74, and ≥ 75 years old in the phase 3 study were 7.4, 7.9, and 8.0 mg/dL, respectively, after sodium phosphate administration. Greater sensitivity of some older individuals cannot be ruled out; therefore, OsmoPrep Tablets should be used with caution in geriatric patients.

Sodium phosphate is known to be substantially excreted by the kidney, and the risk of adverse reactions with sodium phosphate may be greater in patients with impaired renal function. Since geriatric patients are more likely to have impaired renal function, consider performing baseline and post-colonoscopy labs (phosphate, calcium, potassium, sodium, creatinine, and BUN) in these patients (see WARNINGS). It is recommended that patients receiving OsmoPrep be advised to adequately hydrate before, during, and after the use of OsmoPrep.

ADVERSE REACTIONS

Abdominal bloating, abdominal pain, nausea, and vomiting were the most common adverse events reported with the use of OsmoPrep Tablets. Dizziness and headache were reported less frequently. Since diarrhea was considered as a part of the efficacy of OsmoPrep, diarrhea was not defined as an adverse event in the clinical studies. Table 2 shows the most common adverse events associated with the use of 48 grams of OsmoPrep, 60 grams of OsmoPrep, and 60 grams of Visicol in the colon preparation trials (n=931).

Table 2: Frequency of Adverse Events of Any Severity
Occurring in Greater Than 3% of Patients in the OsmoPrep
Trials
 | OsmoPrep 32 tabs (48 g) N=272 | OsmoPrep 40 tabs (60 g) N=265 | Visicol 40 tabs (60 g) N=268
Bloating | 31% | 39% | 41%
Nausea | 26% | 37% | 30%
Abdominal Pain | 23% | 24% | 25%
Vomiting | 4% | 10% | 9%

Postmarketing Experience

In addition to adverse events reported from clinical trials, the following adverse events have been identified during post-approval use of OsmoPrep. Because they are reported voluntarily from a population of unknown size, estimates of frequency cannot be made. These events have been chosen for inclusion due to either their seriousness, frequency of reporting or causal connection to OsmoPrep, or a combination of these factors.

General: Hypersensitivity reactions including anaphylaxis, rash, pruritus, urticaria, throat tightness, bronchospasm, dyspnea, pharyngeal edema, dysphagia, paresthesia and swelling of the lips and tongue, and facial swelling.

Cardiovascular: Arrhythmias

Nervous system: Seizures

Renal: Renal impairment, increased blood urea nitrogen (BUN), increased creatinine, acute renal failure, acute phosphate nephropathy, nephrocalcinosis, and renal tubular necrosis.

DRUG ABUSE AND DEPENDENCE

Laxatives and purgatives (including OsmoPrep) have the potential for abuse by bulimia nervosa patients who frequently have binge eating and vomiting.

OVERDOSAGE

There have been no reported cases of overdosage with OsmoPrep Tablets. Purposeful or accidental ingestion of more than the recommended dosage of OsmoPrep Tablets might be expected to lead to severe electrolyte disturbances, including hyperphosphatemia, hypocalcemia, hypernatremia, or hypokalemia, as well as dehydration and hypovolemia, with attendant signs and symptoms of these disturbances. Certain severe electrolyte disturbances resulting from overdose may lead to cardiac arrhythmias, seizure, renal failure, and death. The patient who has taken an overdosage should be monitored carefully, and treated symptomatically for complications until stable.

DOSAGE AND ADMINISTRATION

The recommended dose of OsmoPrep Tablets for colon cleansing for adult patients is 32 tablets (48 grams of sodium phosphate) taken orally with a total of 2 quarts of clear liquids in the following manner:

The evening before the colonoscopy procedure: Take 4 OsmoPrep Tablets with 8 ounces of clear liquids every 15 minutes for a total of 20 tablets.
On the day of the colonoscopy procedure: Starting 3-5 hours before the procedure, take 4 OsmoPrep Tablets with 8 ounces of clear liquids every 15 minutes for a total of 12 tablets.

Patients should be advised of the importance of taking the recommended fluid regimen. It is recommended that patients receiving OsmoPrep be advised to adequately hydrate before, during, and after the use of OsmoPrep.

Patients should not use OsmoPrep for colon cleansing within seven days of previous administration. No additional enema or laxative is required, and patients should be advised NOT to take additional agents, particularly those containing sodium phosphate.

HOW SUPPLIED

OsmoPrep Tablets are supplied in child-resistant bottles containing 32 tablets. Each tablet contains 1.102 g sodium phosphate monobasic monohydrate, USP and 0.398 g sodium phosphate dibasic anhydrous, USP for a total of 1.5 g of sodium phosphate per tablet.

NDC 54868-5889-1 | Bottles of 04
NDC 54868-5889-0 | Bottles of 32

Rx only.

Store at 25°C (77°F); excursions permitted to 15-30°C (59-86°F) [See USP Controlled Room Temperature]. Discard any unused portion.

Manufactured by:
WellSpring Pharmaceutical Canada Corp.
Oakville, Ontario Canada L6H 1M5
for:
Salix Pharmaceuticals, Inc.
Morrisville, NC 27560
Made in Canada

VENART-30-4/Mar. 2009

Product protected by US Patent No. 5,616,346 and other pending applications.

Relabeling and Repackaging by:
Physicians Total Care, Inc.
Tulsa, OK 74146

Medication Guide

OsmoPrep® (AhZ-MŌ-prěp) (sodium phosphate monobasic monohydrate, USP and sodium phosphate dibasic anhydrous, USP) Tablets

Read the Medication Guide that comes with OsmoPrep before you take it and each time you take it. This Medication Guide does not take the place of talking with your doctor about your medical condition or your treatment. If you have any questions about OsmoPrep, ask your doctor or pharmacist.

What is the most important information I should know about OsmoPrep?

OsmoPrep can cause serious side effects, including:

Serious kidney problems. Rare, but serious kidney problems can happen in people who take medicines made with sodium phosphate, including OsmoPrep, to clean your colon before colonoscopy. These kidney problems can sometimes lead to kidney failure or the need for dialysis for a long time. These problems often happen within a few days, but sometimes may happen several months after taking OsmoPrep.

Conditions that can make you more at risk for having serious kidney problems with OsmoPrep include if you:

- lose too much body fluid (dehydration)
- have slow moving bowels
- have bowels blocked with stool (constipation)
- have severe stomach pain or bloating
- have any disease that causes bowel irritation (colitis)
- have kidney disease
- have heart failure
- take water pills or non-steroidal anti-inflammatory drugs (NSAIDS)

Your age may also affect your risk for having kidney problems with OsmoPrep.

Before you start taking OsmoPrep tell your doctor if you:

- have kidney problems.
- take any medicines for blood pressure, heart disease, or kidney disease.

Severe fluid loss. People who take medicines that contain sodium phosphate can have severe loss of body fluid, with severe changes in body salts in the blood, and abnormal heart rhythms. These problems can lead to death.

Tell your doctor if you have any of these symptoms of loss of too much body fluid (dehydration) while taking OsmoPrep:

- vomiting
- dizziness
- urinating less often than normal
- headache

See “What are the possible side effects of OsmoPrep?” for more information about side effects.

What is OsmoPrep?

OsmoPrep is a prescription medicine used in adults 18 years and older, to clean your colon before a colonoscopy. OsmoPrep cleans your colon by causing you to have diarrhea. Cleaning your colon helps your doctor see the inside of your colon more clearly during the colonoscopy.

It is not known if OsmoPrep is safe and works in children under age 18.

Who should not take OsmoPrep?
Do not take OsmoPrep if:

- you have had a kidney biopsy that shows you have kidney problems because of too much phosphate
- you are allergic to sodium phosphate salts or any of the ingredients in OsmoPrep. See the end of this Medication Guide for a list of ingredients in OsmoPrep.

What should I tell my doctor before taking OsmoPrep?
Before taking OsmoPrep, tell your doctor about all of your medical conditions, including if you have:

- any of the medical conditions listed in the section “What is the most important information I should know about OsmoPrep?"
- irritation of the bowel (colitis). OsmoPrep can cause symptoms of irritable bowel disease to flare-up.
- damage to your bowels
- problems with abnormal heart beat
- had a recent heart attack or have other heart problems
- symptoms of too much body fluid loss (dehydration) including vomiting, dizziness, urinating less often than normal, or headache)
- had stomach surgery
- a history of seizures
- if you drink alcohol
- are on a low salt diet
- are pregnant. It is not known if OsmoPrep will harm your unborn baby.

Tell your doctor about all the medicines you take, including prescription and non-prescription medicines, vitamins, and herbal supplements. Any medicine that you take close to the time that you take OsmoPrep may not work as well. Especially tell your doctor if you take:

- water pills (diuretics)
- medicines for blood pressure or heart problems
- medicines for kidney damage
- medicines for pain, such as aspirin or a non-steroidal anti-inflammatory drug (NSAID)
- a medicine for seizures
- a laxative for constipation in the last 7 days. You should not take another medicine that contains sodium phosphate while you take OsmoPrep.

Ask your doctor if you are not sure if your medicine is listed above.

Know the medicines you take. Keep a list of your medicines to show your doctor or pharmacist when you get a new prescription.

How should I take OsmoPrep?

- Take OsmoPrep exactly as prescribed by your doctor.
- It is important for you to drink clear liquids before, during, and after taking OsmoPrep. This may help prevent kidney damage. Examples of clear liquids are water, flavored water, lemonade (no pulp), ginger ale or apple juice. Do not drink any liquids colored purple or red.

You must read, understand, and follow these instructions to take OsmoPrep the right way:

On the evening before your colonoscopy you will take a total of 20 OsmoPrep tablets, as follows:

1. Take 4 OsmoPrep tablets with 8 ounces of clear liquids.
2. Wait 15 minutes.
3. Take 4 more OsmoPrep tablets with 8 ounces of clear liquids.
4. Repeat steps 2 and 3 above, three more times. Make sure you wait 15 minutes after each time.

On the day of your colonoscopy you will take a total of 12 OsmoPrep tablets, starting about 3 to 5 hours before your colonoscopy, as follows:

1. Take 4 OsmoPrep tablets with 8 ounces of clear liquids.
2. Wait 15 minutes.
3. Take 4 more OsmoPrep tablets with 8 ounces of clear liquids.
4. Repeat steps 2 and 3 one more time.

Tell your doctor if you have any of these symptoms while taking OsmoPrep:

- vomiting, dizziness, or if you urinate less often than normal. These may be signs that you have lost too much fluid while taking OsmoPrep.
- trouble drinking clear fluids
- severe stomach cramping, bloating, nausea, or headache.

If you take too much OsmoPrep, call your doctor or get medical help right away.

What should I avoid while taking OsmoPrep?

- You should not take other laxatives or enemas made with sodium phosphate, while taking OsmoPrep.
- You should not use OsmoPrep if you have already used it in the last 7 days.

What are the possible side effects of OsmoPrep?

OsmoPrep can cause serious side effects, including:

- See “What is the most important information I should know about OsmoPrep?”
- Seizures or fainting (black-outs). People who take a medicine that contains sodium phosphate, such as OsmoPrep, can have seizures or faint (become unconscious) even if they have not had seizures before. Tell your doctor right away if you have a seizure or faint while taking OsmoPrep
- Abnormal heart beat (arrhythmias)
- changes in your blood levels of calcium, phosphate, potassium, sodium

The most common side effects of OsmoPrep are:

- bloating
- stomach area (abdominal) pain
- nausea
- vomiting

These are not all the possible side effects of OsmoPrep. For more information, ask your doctor or pharmacist.

Call your doctor for medical advice about side effects. You may report side effects to FDA at 1-800-FDA-1088.

How do I store OsmoPrep?

- Store OsmoPrep at room temperature, between 59° F to 86° F (15° C to 30° C).
- Throw away any OsmoPrep that is not needed.
- Keep OsmoPrep and all medicines out of the reach of children.

General information about OsmoPrep

Medicines are sometimes prescribed for purposes other than those listed in a Medication Guide. Do not use OsmoPrep for a condition for which it was not prescribed. Do not give OsmoPrep to other people, even if they have the same symptoms that you have. It may harm them.

This Medication Guide summarizes the most important information about OsmoPrep. If you would like more information about OsmoPrep, talk with your doctor or pharmacist. You can ask your doctor or pharmacist for information that is written for healthcare professionals. For more information, call 1-866-669-7597 (toll-free) or go to www.Salix.com.

What are the ingredients in OsmoPrep?

Active ingredients: sodium phosphate monobasic monohydrate and sodium phosphate dibasic anhydrous

Inactive ingredients: polyethylene glycol 8000 and magnesium stearate

This Medication Guide has been approved by the U.S. Food and Drug Administration.

Revised March 2009

Salix Pharmaceuticals, Inc.
Morrisville, NC 27560, USA

This Medication Guide has been approved by the U.S. Food and Drug Administration.

VENART-30-4/Mar 2009

PRINCIPAL DISPLAY PANEL

OsmoPrep®
(sodium phosphate monobasic monohydrate, USP
and sodium phosphate dibasic anhydrous, USP) Tablets